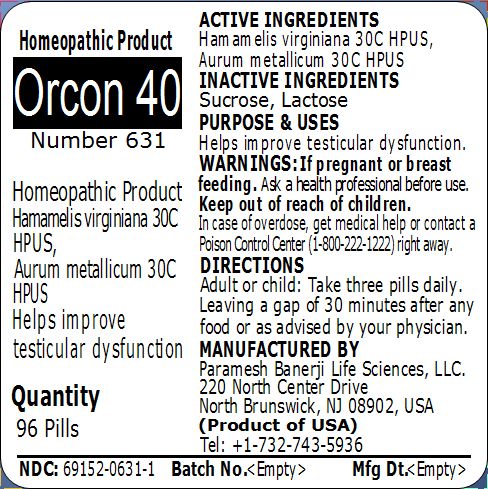 DRUG LABEL: Orcon 40 Number 631
NDC: 69152-0631 | Form: PELLET
Manufacturer: Paramesh Banerji Life Sciences LLC
Category: homeopathic | Type: HUMAN OTC DRUG LABEL
Date: 20150211

ACTIVE INGREDIENTS: HAMAMELIS VIRGINIANA ROOT BARK/STEM BARK 30 [hp_C]/1 1; GOLD 30 [hp_C]/1 1
INACTIVE INGREDIENTS: SUCROSE; LACTOSE

Active Ingredients

Hamamelis virginiana 30C HPUS, Aurum metallicum 30C HPUS

Inactive Ingredients

Sucrose, Lactose

Purpose

Helps improve testicular dysfunction

Uses

Helps improve testicular dysfunction

Warnings

If pregnant or breast feeding ask a health professional before use.

Keep out of reach of children. In case of overdose, get medical help or contact a Poison Control Center (1-800-222-1222) right away.

Direction

Adult or child: Take three pills daily. Leaving a gap of 30 minutes after any food or as advised by your physician.

Manufactured by

Paramesh Banerji Life Sciences, LLC

220 North Center Drive

North Brunswick, NJ 08902, USA

Product of USA

Tel: +1-732-743-5936

Principal Display Panel

Homeopathic Product

Orcon 40

Number 631

Homeopathic Product

Hamamelis virginiana 30C HPUS, Aurum metallicum 30C HPUS

Helps improve testicular dysfunction

Quantity

96 Pills